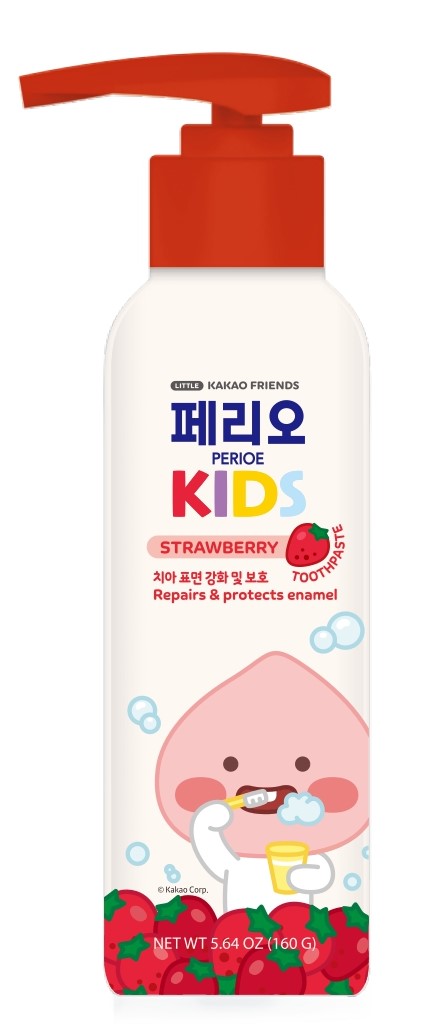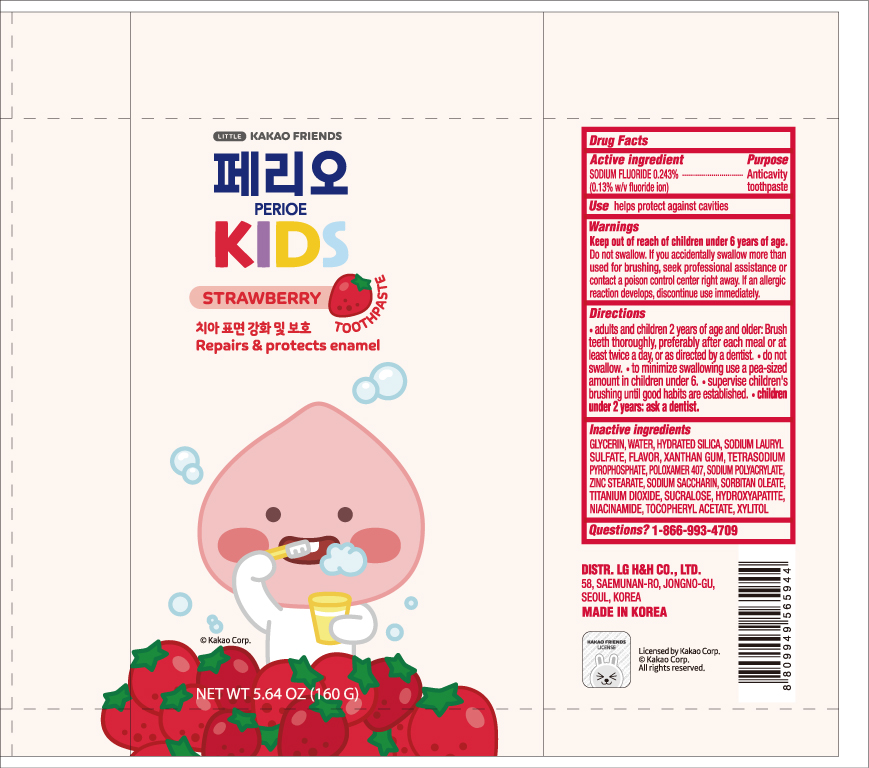 DRUG LABEL: PERIOE KAKAO KIDS
NDC: 53208-461 | Form: PASTE, DENTIFRICE
Manufacturer: LG HOUSEHOLD & HEALTH CARE LTD.
Category: otc | Type: HUMAN OTC DRUG LABEL
Date: 20251028

ACTIVE INGREDIENTS: SODIUM FLUORIDE 1.3 mg/1 g
INACTIVE INGREDIENTS: SUCRALOSE; ZINC STEARATE; NIACINAMIDE; HYDROXYAPATITE; WATER; TETRASODIUM PYROPHOSPHATE; SODIUM LAURYL SULFATE; ALPHA-TOCOPHEROL ACETATE; HYDRATED SILICA; XANTHAN GUM; POLOXAMER 407; SODIUM SACCHARIN; XYLITOL; GLYCERIN; SORBITAN OLEATE; TITANIUM DIOXIDE; SODIUM POLYACRYLATE (8000 MW)

PERIOE KAKAO KIDS STRAWBERRY TOOTHPASTE

Active Ingredients

Sodium Fluoride 0.243%

(0.13% w/v fluoride ion)

Purpose

Anticavity toothpaste

Use

helps protect against cavities

WARNINGS

Keep out of reach of children under 6 years of age.

Directions

Do not swallow. If you accidentally swallow more than used for brushing, seek professional assistance or contact a poison control center right away. If an allergic reaction develops, discontinue use immediately.

Directions

- adults and children 2 years of age and older: Brush teeth thoroughly, preferably after each meal or at least twice a day, or as directly by a dentist.
- do not swallow.
- to minimize swallowing use a pea-sized amount in children under 6.
- supervise children's brushing until good habits are established.
- children under 2 years: ask a dentist.

Inactive ingredients

GLYCERIN, WATER, HYDRATED SILICA, SODIUM LAURYL SULFATE, FLAVOR, XANTHAN GUM, TETRASODIUM PYROPHOSPHATE, POLOXAMER 407, SODIUM POLYACRYLATE, ZINC STEARATE, SODIUM SACCHARIN, SORBITAN OLEATE, TITANIUM DIOXIDE, SUCRALOSE, HYDROXYAPATITE, NIACINAMIDE, TOCOPHERYL ACETATE, XYLITOL

Questions?

1-866-993-4709